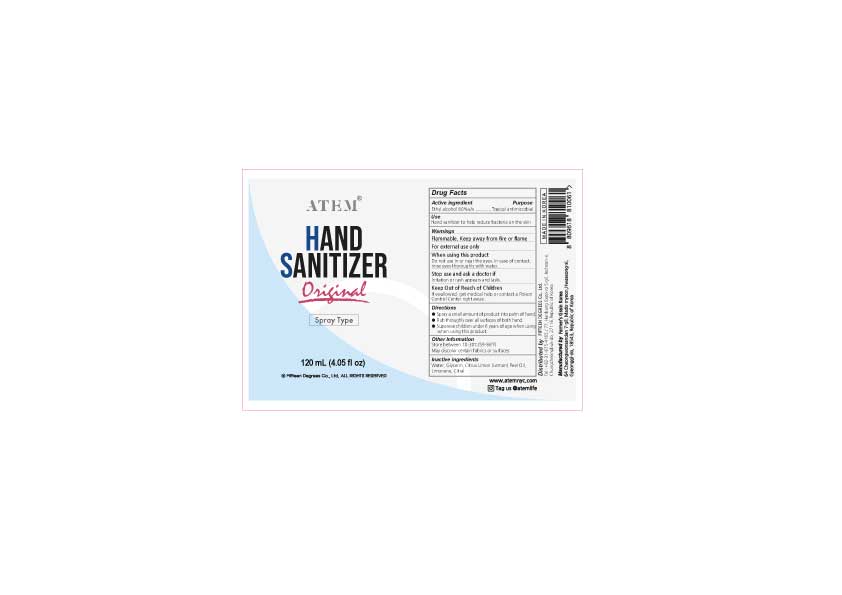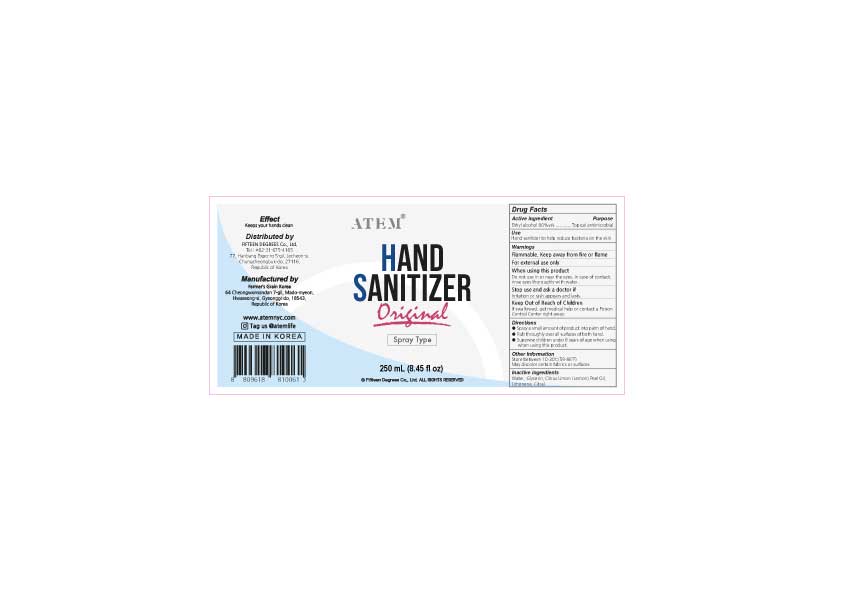 DRUG LABEL: Hand Sanitizer
NDC: 74752-784 | Form: SPRAY
Manufacturer: FARMER'S GRAIN KOREA LTD
Category: otc | Type: HUMAN OTC DRUG LABEL
Date: 20210109

ACTIVE INGREDIENTS: ALCOHOL 80 mL/100 mL
INACTIVE INGREDIENTS: GLYCERIN 1.45 mL/100 mL; WATER 18.45 mL/100 mL; LEMON OIL 0.0323 mL/100 mL; CITRAL 0.0017 mL/100 mL

Hand Sanitizer Farmer Grain 80% alcohol

Active Ingredient(s)

Alcohol 80% v/v. Purpose: Topical Antimicrobial

Purpose

Topical Antimicrobial

Use

Hand Sanitizer to help reduce bacteria on the skin.

Warnings

For external use only. Flammable. Keep away from heat or flame

When using this product, do not use in or near eyes. In case of contact, rinse eyes thoroughly with water.

Stop use and ask a doctor if irritation or rash appears and lasts.

Keep out of reach of children. If swallowed, get medical help or contact a Poison Control Center right away.

Directions

- Spray a small amount of product into palm of hand.
- Rub thoroughly over all surfaces of both hands.
- Supervise children under 6 years of age when using this product.

Other information

- Store between 10-30C (59-86F)
- May discolor certain fabrics or surfaces

Inactive ingredients

water, glycerin, citrus limon (lemon) peel oil, limonene, citral

Package Label - Principal Display Panel

20 mL NDC: 74752-784-12

250 mL NDC: 74752-784-25